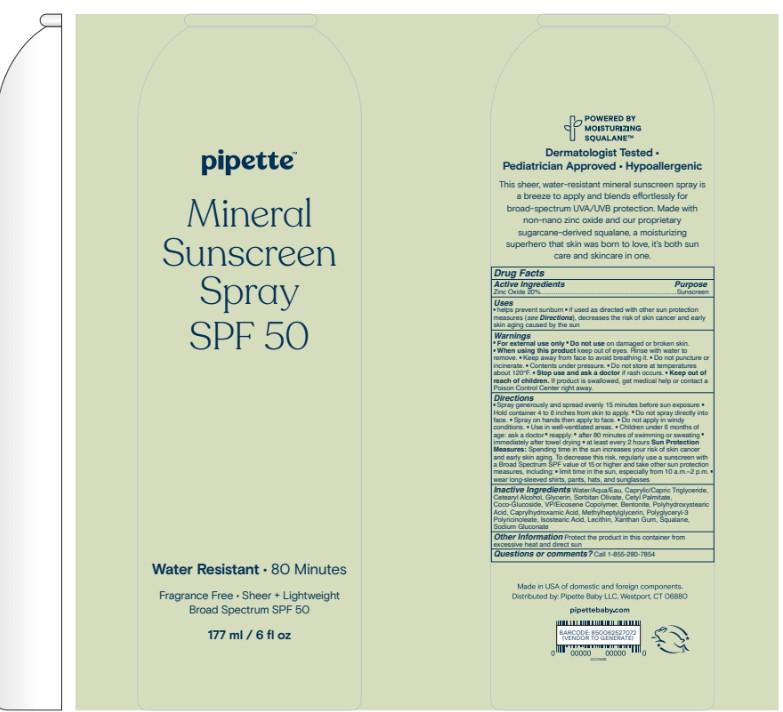 DRUG LABEL: Pipette Mineral Sunscreen SPF 50
NDC: 84723-006 | Form: AEROSOL, SPRAY
Manufacturer: Pipette LLC
Category: otc | Type: HUMAN OTC DRUG LABEL
Date: 20250801

ACTIVE INGREDIENTS: ZINC OXIDE 20 mg/1 mL
INACTIVE INGREDIENTS: SORBITAN OLIVATE; WATER; COCO-GLUCOSIDE; VINYLPYRROLIDONE/EICOSENE COPOLYMER; CAPRYLIC/CAPRIC TRIGLYCERIDE; ISOSTEARIC ACID; XANTHAN GUM; GLYCERIN; POLYGLYCERYL-3 PENTARICINOLEATE; CETEARYL ALCOHOL; BENTONITE; POLYHYDROXYSTEARIC ACID (2300 MW); SQUALANE; CAPRYLHYDROXAMIC ACID; SODIUM GLUCONATE; CETYL PALMITATE; LECITHIN, SUNFLOWER

Active Ingredients

Zinc Oxide - 20%

Uses

helps prevent sunburn . if used as directed with other sun protection
measures (see Directions), decreases the risk of skin cancer and early
skin aging caused by the sun

Warnings

. For external use only " Do not use on damaged or broken skin.
. When using this product keep out of eyes. Ainse with water to
remove. . Keep away from face to avoid breathing it. . Do not puncture or
incinerate. . Contents under pressure. . Do not store at temperatures
about 120"F .. Stop use and ask a doctor if rash occurs. . Keep out of
reach of children. If product is swallowed, get medical help or contact a
Poison Control Center right away.

Directions

.Spray generously and spread evenly 15 minutes before sun exposure .
Hold container 4 to 6 inches from skin to apply. " Do not spray directly into
face. . Spray on hands then apply to face. . Do not apply in windy
conditions. . Use in well-vertilated areas. . Children under 6 months of
age: ask a doctor" reapply:" after 80 minutes of swimming or sweating"
immediately after towel drying . at least every 2 hours Sun Protection
Measures: Spending time in the sun increases your risk of skin cancer
and early skin aging. To decrease this risk, regularly use a sunscreen with
a Broad Spectrum SPF value of 15 or higher and take other sun protection
measures, including: . limit time in the sun, especially from 10 a.m .- 2 p.m ..
wear long-sleeved shirts, pants, hats, and sunglasses

Other Information

Protect the product in this container from
excessive heat and direct sun

Inactive Ingredients

Water/Aqua/Eau, Caprylic/Capric Triglyceride,
Cetearyl Alcohol, Glycerin, Sorbitan Olivate, Cetyl Palmitate,
Coco-Glucoside, VP/Eicosene Copalymer, Bentonite, Polyhydroxystearic
Acid, Caprylhydroxamic Acid, Methylheptylglycerin, Polyglyceryl-3
Polyricinoleate, Isostearic Acid, Lecithin, Xanthan Gum, Squalane,
Sodium Gluconate

Questions or comments?

Call 1-855-280-7854

Keep out of reach of children

Purpose

Sunscreen